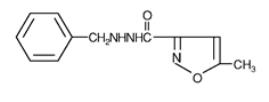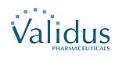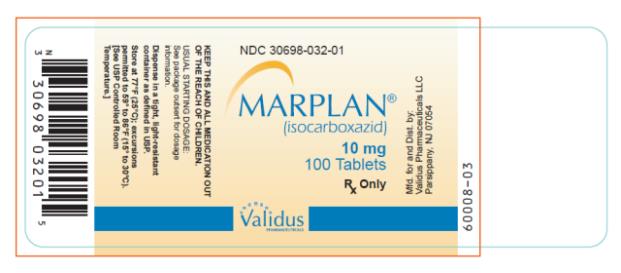 DRUG LABEL: Marplan
NDC: 30698-032 | Form: TABLET
Manufacturer: Validus Pharmaceuticals LLC
Category: prescription | Type: HUMAN PRESCRIPTION DRUG LABEL
Date: 20230717

ACTIVE INGREDIENTS: ISOCARBOXAZID 10 mg/1 1
INACTIVE INGREDIENTS: LACTOSE, UNSPECIFIED FORM; STARCH, CORN; POVIDONE; D&C RED NO. 27; FD&C YELLOW NO. 6; MAGNESIUM STEARATE

Marplan

brand of isocarboxazid tablets

BOXED WARNING

Suicidality and Antidepressant Drugs

Antidepressants increased the risk compared to placebo of suicidal thinking and behavior (suicidality) in children, adolescents, and young adults in short-term studies with Major Depressive Disorder (MDD) and other psychiatric disorders. Anyone considering the use of Marplan or any other antidepressant in a child, adolescent or young adult must balance this risk with the clinical need. Short-term studies did not show an increase in the risk of suicidality with antidepressants compared to placebo in adults beyond age 24; there was a reduction in risk with antidepressants compared to placebo in adults aged 65 and older. Depression and certain other psychiatric disorders are themselves associated with increases in the risk of suicide. Patients of all ages who are started on antidepressant therapy should be monitored appropriately and observed closely for clinical worsening, suicidality, or unusual changes in behavior. Families and caregivers should be advised of the need for close observation and communication with the prescriber. Marplan is not approved for use in pediatric patients (see Warnings: Clinical Worsening and Suicide Risk, Precautions: Information for Patients, and Precautions: Pediatric Use).

Pooled analyses of short-term (4 to 16 weeks) placebo-controlled trials of 9 antidepressant drugs (SSRIs and others) in children and adolescents with major depressive disorder (MDD), obsessive compulsive disorder (OCD), or other psychiatric disorders (a total of 24 trials involving over 4400 patients) have revealed a greater risk of adverse events representing suicidal thinking or behavior (suicidality) during the first few months of treatment in those receiving antidepressants. The average risk of such events in patients receiving antidepressants was 4%, twice the placebo risk of 2%. No suicides occurred in these trials.

DESCRIPTION

Marplan (isocarboxazid), a monoamine oxidase inhibitor, is available for oral administration in 10-mg tablets. Each tablet also contains lactose, corn starch, povidone, D&C Red No. 27, FD&C Yellow No. 6, and magnesium stearate. Chemically, isocarboxazid is 5-methyl-3-isoxazolecarboxylic acid 2-benzylhydrazide. The structural formula is:

Isocarboxazid is a colorless, crystalline substance with very little taste.

CLINICAL PHARMACOLOGY

Pharmacodynamics

Isocarboxazid is a non-selective hydrazine monoamine oxidase (MAO) inhibitor. In vivo and in vitro studies demonstrated inhibition of MAO in the brain, heart, and liver. The mechanism by which MAO inhibitors act as antidepressants is not fully understood, but it is thought to involve the elevation of brain levels of biogenic amines. However, MAO is a complex enzyme system, widely distributed throughout the body, and drugs that inhibit MAO in the laboratory are associated with a number of clinical effects. Thus, it is unknown whether MAO inhibition per se, other pharmacologic actions, or an interaction of both is responsible for the antidepressant effects observed.

Pharmacokinetics

Marplan pharmacokinetic information is not available.

Clinical Efficacy Data

The effectiveness of Marplan was demonstrated in two 6-week placebo-controlled studies conducted in adult outpatients with depressive symptoms that corresponded to the DSM-IV category of major depressive disorder. The patients often also had signs and symptoms of anxiety (anxious mood, panic, and/or phobic symptoms). Patients were initiated with a dose of 10 mg bid, with increases every 2 to 4 days, as tolerated, until a therapeutic effect was achieved, up to a maximum dose of 80 mg/day. Doses were administered on a divided schedule ranging from 2 to 4 times a day. The mean dose overall for both studies was approximately 40 mg/day, with very few patients receiving doses greater than 60 mg/day. In both studies at the end of 6 weeks, patients receiving Marplan had significantly greater reduction in signs and symptoms of depression evaluated by the Hamilton Depression Scale, for both the Total Score and the Depressed Mood Score, than patients who received placebo.

INDICATIONS AND USAGE

Marplan is indicated for the treatment of depression. Because of its potentially serious side effects, Marplan is not an antidepressant of first choice in the treatment of newly diagnosed depressed patients.

The efficacy of Marplan in the treatment of depression was established in 6-week controlled trials of depressed outpatients. These patients had symptoms that corresponded to the DSM-IV category of major depressive disorder; however, they often also had signs and symptoms of anxiety (anxious mood, panic, and/or phobic symptoms) (see CLINICAL PHARMACOLOGY).

A major depressive episode (DSM-IV) implies a prominent and relatively persistent (nearly every day for at least 2 weeks) depressed or dysphoric mood that usually interferes with daily functioning, and includes at least five of the following nine symptoms: depressed mood, loss of interest in usual activities, significant change in weight and/or appetite, insomnia or hypersomnia, psychomotor agitation or retardation, increased fatigue, feelings of guilt or worthlessness, slowed thinking or impaired concentration, and a suicide attempt or suicidal ideation.

The antidepressant effectiveness of Marplan in hospitalized depressed patients, or in endogenomorphically retarded and delusionally depressed patients, has not been adequately studied.

The effectiveness of Marplan in long-term use, that is, for more than 6 weeks, has not been systematically evaluated in controlled trials. Therefore, the physician who elects to use Marplan for extended periods should periodically evaluate the long-term usefulness of the drug for the individual patient.

CONTRAINDICATIONS

Marplan (isocarboxazid) should not be administered in combination with any of the following: MAO inhibitors or dibenzazepine derivatives; sympathomimetics (including amphetamines); some central nervous system depressants (including narcotics and alcohol); antihypertensive, diuretic, antihistaminic, sedative or anesthetic drugs, buproprion HCL, buspirone HCL, dextromethorphan, cheese or other foods with a high tyramine content; or excessive quantities of caffeine.

Marplan (isocarboxazid) should not be administered to any patient with a confirmed or suspected cerebrovascular defect or to any patient with cardiovascular disease, hypertension, or history of headache.

Contraindicated Patient Populations

Hypersensitivity

Marplan should not be used in patients with known hypersensitivity to isocarboxazid.

Cerebrovascular Disorders

Marplan should not be administered to any patient with a confirmed or suspected cerebrovascular defect or to any patient with cardiovascular disease or hypertension.

Pheochromocytoma

Marplan should not be used in the presence of pheochromocytoma, as such tumors secrete pressor substances whose metabolism may be inhibited by Marplan.

Liver Disease

Marplan should not be used in patients with a history of liver disease, or in those with abnormal liver function tests.

Renal Impairment

Marplan should not be used in patients with severe impairment of renal function.

Contraindicated MAOI-Other Drug Combinations

Other MAOI Inhibitors or With Dibenzazepine-Related Entities

Marplan should not be administered together with, or in close proximity to, other MAO inhibitors or dibenzazepine-related entities. Hypertensive crises, severe convulsive seizures, coma, or circulatory collapse may occur in patients receiving such combinations.

In patients being transferred to Marplan from another MAO inhibitor or from a dibenzazepine-related entity, a medication-free interval of at least 1 week should be allowed, after which Marplan therapy should be started using half the normal starting dosage for at least the first week of therapy. Similarly, at least 1 week should elapse between the discontinuation of Marplan and initiation of another MAO inhibitor or dibenzazepine-related entity, or the readministration of Marplan. The following list includes some other MAO inhibitors, dibenzazepine-related entities, and tricyclic antidepressants.

Generic Name | Trademark (Manufacturer)
Other MAO Inhibitors
Furazolidone | Furoxone® (Roberts Laboratories)
Pargyline HCL | Eutonyl® (Abbott Laboratories)
Pargyline HCL and methyclothiazide | Eutron® (Abbott Laboratories)
Phenelzine sulfate | Nardil® (Parke-Davis)
Procarbazine | Matulane® (Roche Laboratories)
Tranylcypromine sulfate | Parnate® (SmithKline Beecham Pharmaceuticals)
Dibenzazepine-Related and Other Tricyclics
Amitriptyline HCL | Elavil® (Zeneca)
 | Endep® (Roche Products)
Perphenazine and amitriptyline HCL | Etrafon® (Schering)
 | Triavil® (Merck Sharp & Dohme)
Clomipramine hydrochloride | Anafranil® (Novartis)
Desipramine HCL | Norpramin® (Hoechst Marion Roussel)
 | Pertofrane® (Rhône-Poulenc Rorer Pharmaceuticals)
Imipramine HCL | Janimine® (Abbott Laboratories)
 | Tofranil® (Novartis)
Nortriptyline HCL | Aventyl® (Eli Lilly & Co.)
 | Pamelor® (Novartis)
Protripyline HCL | Vivactil® (Merck Sharp & Dohme)
Doxepin HCL | Adapin® (Fisons)
 | Sinequan® (Pfizer)
Carbamazepine | Tegretol® (Novartis)
Cyclobenzaprine HCL | Flexeril® (Merck Sharp & Dohme)
Amoxapine | Asendin® (Lederle)
Maprotiline HCL | Ludiomil® (Novartis)
Trimipramine maleate | Surmontil® (Wyeth-Ayerst Laboratories)

Bupropion

The concurrent administration of a MAO inhibitor and buproprion hydrochloride (Wellbutrin®, and Zyban®, Glaxo Wellcome) is contraindicated. At least 14 days should elapse between discontinuation of an MAO inhibitor and initiation of treatment with buproprion hydrochloride.

Selective Serotonin Re-uptake Inhibitors (SSRIs)

Marplan should not be administered in combination with any SSRI. There have been reports of serious, sometimes fatal, reactions (including hyperthermia, rigidity, myoclonus, autonomic instability with possible rapid fluctuations of vital signs, and mental status changes that include extreme agitation and confusion progressing to delirium and coma) in patients receiving fluoxetine (Prozac®, Lilly) in combination with a monoamine oxidase inhibitor (MAOI), and in patients who have recently discontinued fluoxetine and are then started on a MAOI. Some cases presented with features resembling neuroleptic malignant syndrome. Fluoxetine and other SSRIs should therefore not be used in combination with Marplan, or within 14 days of discontinuing therapy with Marplan. As fluoxetine and its major metabolite have very long elimination half-lives, at least 5 weeks should be allowed after stopping fluoxetine before starting Marplan. At least 2 weeks should be allowed after stopping sertraline (Zoloft®, Pfizer) or paroxetine (Paxil®, SmithKline Beecham Pharmaceuticals) before starting Marplan. In addition, there should be an interval of least 10 days between discontinuation of Marplan and initiation of fluoxetine or other SSRIs.

Buspirone

Marplan should not be used in combination with buspirone HCL (Buspar®, Bristol Myers Squibb); several cases of elevated blood pressure have been reported in patients taking MAO inhibitors who were then given buspirone HCL. At least 10 days should elapse between the discontinuation of Marplan and the institution of buspirone HCL. Serious reactions may also occur when MAO inhibitors are given with serotoninergic drugs (e.g., dexfenfluramine, fluoxetine, fluvoxamine, paroxetine, sertraline, citalopram, venlafaxine).

Sympathomimetics

Marplan should not be administered in combination with sympathomimetics, including amphetamines, or with over-the-counter drugs such as cold, hay fever, or weight-reducing preparations that contain vasoconstrictors.

During Marplan therapy, it appears that some patients are particularly vulnerable to the effects of sympathomimetics when the activity of metabolizing enzymes is inhibited. Use of sympathomimetics and compounds such as guanethidine, methyldopa, methylphenidate, reserpine, epinephrine, norepinephrine, phenylalanine, dopamine, levodopa, tyrosine, and tryptophan with Marplan may precipitate hypertension, headache, and related symptoms. The combination of MAO inhibitors and tryptophan has been reported to cause behavioral and neurologic symptoms, including disorientation, confusion, amnesia, delirium, agitation, hypomanic signs, ataxia, myoclonus, hyperreflexia, shivering, ocular oscillations, and Babinski signs.

Meperidine

Meperidine should not be used concomitantly with MAO inhibitors or within 2- or 3-weeks following MAO therapy. Serious reactions have been precipitated with concomitant use, including coma, severe hypertension or hypotension, severe respiratory depression, convulsions, malignant hyperpyrexia, excitation, peripheral vascular collapse, and death. It is thought that these reactions may be mediated by accumulation of 5-HT (serotonin) consequent to MAO inhibition.

Dextromethorphan

Marplan should not be used in combination with dextromethorphan. The combination of MAO inhibitors and dextromethorphan has been reported to cause brief episodes of psychosis or bizarre behavior.

Cheese or Other Foods With a High Tyramine Content

Hypertensive crises have sometimes occurred during Marplan therapy after ingestion of foods with a high tyramine content. In general, patients should avoid protein foods in which aging or protein breakdown is used to increase flavor. In particular, patients should be instructed not to take foods such as cheese (particularly strong or aged varieties), sour cream, Chianti wine, sherry, beer (including non-alcoholic beer), liqueurs, pickled herring, anchovies, caviar, liver, canned figs, raisins, bananas or avocados (particularly if overripe), chocolate, soy sauce, sauerkraut, the pods of broad beans (fava beans), yeast extracts, yogurt, meat extracts, meat prepared with tenderizers, or dry sausage.

Anesthetic Agents

Patients taking Marplan should not undergo elective surgery requiring general anesthesia. Also, they should not be given cocaine or local anesthesia containing sympathomimetic vasoconstrictors. The possible combined hypotensive effects of Marplan and spinal anesthesia should be kept in mind. Marplan should be discontinued at least 10 days before elective surgery.

CNS Depressants

Marplan should not be used in combination with some central nervous system depressants, such as narcotics, barbiturates, or alcohol.

Antihypertensives

Marplan should not be used in combination with antihypertensive agents, including thiazide diuretics. A marked potentiating effect on these drugs has been reported, resulting in hypotension.

Caffeine

Excessive use of caffeine in any form should be avoided in patients receiving Marplan.

WARNINGS TO PHYSICIANS

Clinical Worsening and Suicide Risk

Patients with major depressive disorder (MDD), both adult and pediatric, may experience worsening of their depression and/or the emergence of suicidal ideation and behavior (suicidality) or unusual changes in behavior, whether or not they are taking antidepressant medications, and this risk may persist until significant remission occurs. Suicide is a known risk of depression and certain other psychiatric disorders, and these disorders themselves are the strongest predictors of suicide. There has been a long-standing concern, however, that antidepressants may have a role in inducing worsening of depression and the emergence of suicidality in certain patients during the early phases of treatment. Pooled analyses of short-term placebo-controlled trials of antidepressant drugs (SSRIs and others) showed that these drugs increase the risk of suicidal thinking and behavior (suicidality) in children, adolescents, and young adults (ages 18 to 24) with major depressive disorder (MDD) and other psychiatric disorders. Short-term studies did not show an increase in the risk of suicidality with antidepressants compared to placebo in adults beyond age 24; there was a reduction with antidepressants compared to placebo in adults aged 65 and older.

The pooled analyses of placebo-controlled trials of nine antidepressant drugs (SSRIs) and others) in children and adolescents with MDD, Obsessive compulsive disorder (OCD), or other psychiatric disorders included a total of 24 short-term trials of 9 antidepressant drugs in over 4400 patients. The pooled analyses of placebo-controlled trials in adults with MDD or other psychiatric disorders included 295 short-term trials (median duration of 2 months) of 11 antidepressant drugs in over 77,000 patients. There was considerable variation in risk among drugs, but a tendency toward an increase in the younger patients `for almost all drugs studied. There were differences in absolute risk of suicidality across the different indications, with the highest incidence in MDD. The risk differences (drug vs. placebo), however, were relatively stable within age strata and across indications. These risk differences (drug-placebo difference in the number of cases of suicidality per 1000 patients treated) are provided in Table 1.

Table 1
Age Range | Drug-Placebo Difference in Number of Cases of Suicidality Per 1000 Patients Treated
 | Increases Compared to Placebo
<18 | 14 additional cases
18 to 24 | 5 additional cases
 | Decreases Compared to Placebo
25 to 64 | 1 fewer case
>65 | 6 fewer cases

No suicides occurred in any of the pediatric trials. There were suicides in the adult trials, but the number was not sufficient to reach any conclusion about drug effect on suicide.

It is unknown whether the suicidality risk extends to longer-term use, i.e., beyond several months. However, there is substantial evidence from placebo-controlled maintenance trials in adults with depression that the use of antidepressants can delay the recurrence of depression.

All patients being treated with antidepressants for any indication should be monitored appropriately and observed closely for clinical worsening, suicidality, and unusual changes in behavior, especially during the initial few months of a course of drug therapy, or at times of dose changes, either increases or decreases.

The following symptoms, anxiety, agitation, panic attacks, insomnia, irritability, hostility, aggressiveness, impulsivity, akathisia (psychomotor restlessness), hypomania, and mania, have been reported in adult and pediatric patients being treated with antidepressants for major depressive disorder as well as for other indications, both psychiatric and nonpsychiatric. Although a casual link between the emergence of such symptoms and either the worsening of depression and/or the emergence of suicidal impulses has not been established, there is concern that such symptoms may represent precursors to emerging suicidality.

Consideration should be given to changing the therapeutic regimen, including possibly discontinuing the medication, in patients whose depression is persistently worse, or who are experiencing emergent suicidality or symptoms that might be precursors to worsening depression or suicidality, especially if these symptoms are severe, abrupt in onset or were not part of the patient’s presenting symptoms.

Families and caregivers of patients being treated with antidepressants for major depressive disorder or other indications both psychiatric and nonpsychiatric, should be alerted about the need to monitor patients for the emergence of agitation, irritability, unusual changes in behavior and the other symptoms described above, as well as the emergence of suicidality, and to report such symptoms immediately to health care providers. Such monitoring should include daily observation by families and caregivers. Prescriptions for MARPLAN should be written for the smallest quantity of tablets consistent with good patient management, in order to reduce the risk of overdose.

Screening Patients for Bipolar Disorder

A major depressive episode may be the initial presentation of bipolar disorder. It is generally believed (though not established in controlled trials) that treating such an episode with an antidepressant alone may increase the likelihood of precipitation of a mixed/manic episode in patients at risk for bipolar disorder. Whether any of these symptoms described above represent such a conversion is unknown. However, prior to initiating treatment with an antidepressant, patients with depressive symptoms should be adequately screened to determine if they are at risk for bipolar disorder; such screening should include a detailed psychiatric history, including a family history of suicide, bipolar disorder, and depression. It should be noted that MARPLAN is not approved for use in treating bipolar depression.

WARNINGS: Second Line Status

Marplan can cause serious side effects. It is not recommended as initial therapy but should be reserved for patients who have not responded satisfactorily to other antidepressants.

Hypertensive Crises

The most important reaction associated with MAO inhibitors is the occurrence of hypertensive crises, which have sometimes been fatal, resulting from the co-administration of MAOIs and certain drugs and foods (see CONTRAINDICATIONS).

These crises are characterized by some or all of the following symptoms: occipital headache which may radiate frontally, palpitation, neck stiffness or soreness, nausea or vomiting, sweating (sometimes with fever and sometimes with cold, clammy skin), and photophobia. Either tachycardia or bradycardia may be present, and associated constricting chest pain and dilated pupils may occur. Intracranial bleeding, sometimes fatal, has been reported in association with the increase in blood pressure.

Blood pressure should be followed closely in patients taking Marplan to detect any pressor response.

Therapy should be discontinued immediately if palpitations or frequent headaches occur during Marplan therapy as these symptoms may be prodromal of a hypertensive crisis.

If a hypertensive crisis occurs, Marplan should be discontinued, and therapy to lower blood pressure should be instituted immediately. Although there has been no systematic study of treatment of hypertensive crisis, phentolamine (available as Regitine®, Novartis) has been used and is recommended at a dosage of 5 mg IV. Care should be taken to administer the drug slowly in order to avoid producing an excessive hypotensive effect. Fever should be managed by means of external cooling. Other symptomatic and supportive measures may be desirable in particular cases. Parenteral reserpine should not be used.

Warnings to the Patient

Patients should be instructed to report promptly the occurrence of headache or other unusual symptoms, i.e., palpitation and/or tachycardia, a sense of constriction in the throat or chest, sweating, dizziness, neck stiffness, nausea, or vomiting. Patients should be warned against eating the foods listed under CONTRAINDICATIONS while on Marplan therapy and should also be told not to drink alcoholic beverages. The patient should also be warned about the possibility of hypotension and faintness, as well as drowsiness sufficient to impair performance of potentially hazardous tasks, such as driving a car or operating machinery.

Patients should also be cautioned not to take concomitant medications, whether prescription or over-the-counter drugs such as cold, hay fever, or weight-reducing preparations, without the advice of a physician. They should be advised not to consume excessive amounts of caffeine in any form. Likewise, they should inform their physicians and their dentist about the use of Marplan.

Limited Experience With Marplan at Higher Doses

Because of the limited experience with systematically monitored patients receiving Marplan at the higher end of the currently recommended dose range of up to 60 mg/day, caution is indicated in patients for whom a dose of 40 mg/day is exceeded (see ADVERSE REACTIONS).

PRECAUTIONS

Information for Patients

Prescribers or other health professionals should inform patients, their families, and their caregivers about the benefits and risks associated with treatment with Marplan and should counsel them in its appropriate use. A patient Medication Guide about “Antidepressant Medications, Depression and Other Serious Mental Illness, and Suicidal Thoughts and Actions” is available for Marplan. The prescriber or health professional should instruct patients, their families, and their caregivers to read the Medication Guide and should assist them in understanding its contents. Patients should be given the opportunity to discuss the contents of the Medication Guide and to obtain answers to any questions they may have. The complete text of the Medication Guide is reprinted at the end of this document.

Patients should be advised of the following issues and asked to alert their prescriber if these occur while taking Marplan.

Clinical Worsening and Suicide Risk

Patients, their families, and their caregivers should be encouraged to be alert to the emergence of anxiety, agitation, panic attacks, insomnia, irritability, hostility, aggressiveness, impulsivity, akathisia (psychomotor restlessness), hypomania, mania, other unusual changes in behavior, worsening of depression, and suicidal ideation, especially early during antidepressant treatment and when the dose is adjusted up or down. Families and caregivers of patients should be advised to observe for the emergence of such symptoms on a day-to-day basis, since changes may be abrupt. Such symptoms should be reported to the patient’s prescriber or health professional, especially if they are severe, abrupt in onset, or were not part of the patient’s presenting symptoms. Symptoms such as these may be associated with an increased risk for suicidal thinking and behavior and indicate a need for very close monitoring and possibly changes in the medication.

Pediatric Use - Safety and effectiveness in the pediatric population have not been established (see BOX WARNING and WARNINGS-Clinical Worsening and Suicide Risk).

Anyone considering the use of Marplan in a child or adolescent must balance the potential risks with the clinical need.

General

Hypotension

Hypotension has been observed during Marplan therapy. Symptoms of postural hypotension are seen most commonly, but not exclusively, in patients with preexistent hypertension; blood pressure usually returns rapidly to pretreatment levels upon discontinuation of the drug. Dosage increases should be made more gradually in patients showing a tendency toward hypotension at the beginning of therapy. Postural hypotension may be relieved by having the patient lie down until blood pressure returns to normal. When Marplan is combined with phenothiazine derivatives or other compounds known to cause hypotension, the possibility of additive hypotensive effects should be considered.

Lower Seizure Threshold

Because Marplan lowers the convulsive threshold in some animal experiments, suitable precautions should be taken if epileptic patients are treated. Marplan appears to have varying effects in epileptic patients; while some have a decrease in frequency of seizures, others have more seizures.

Drugs that lower the seizure threshold, including MAO inhibitors, should not be used with Amipaque® (metrizamide, Sanofi Winthrop Pharmaceuticals). As with other MAO inhibitors, Marplan should be discontinued at least 48 hours before myelography and should not be resumed for at least 24 hours postprocedure.

Hepatotoxicity

There is a low incidence of altered liver function or jaundice in patients treated with Marplan. In the past, it was difficult to differentiate most cases of drug-induced hepatocellular jaundice from viral hepatitis although this is no longer true. Periodic liver chemistry tests should be performed during Marplan therapy; use of the drug should be discontinued at the first sign of hepatic dysfunction or jaundice.

Suicide

In depressed patients, the possibility of suicide should always be considered and adequate precautions taken. Exclusive reliance on drug therapy to prevent suicidal attempts is unwarranted, as there may be a delay in the onset of therapeutic effect or an increase in anxiety or agitation. Also, some patients fail to respond to drug therapy or may respond only temporarily. The strictest supervision, and preferably hospitalization, are required.

Use in Patients With Concomitant Illness

MAO inhibitors can suppress anginal pain that would otherwise serve as a warning of myocardial ischemia.

In patients with impaired renal function, Marplan should be used cautiously to prevent accumulation.

Some MAO inhibitors have contributed to hypoglycemic episodes in diabetic patients receiving insulin or glycemic agents. Marplan should therefore be used with caution in diabetics using these drugs.

Marplan may aggravate coexisting symptoms in depression, such as anxiety and agitation.

Use Marplan with caution in hyperthyroid patients because of their increased sensitivity to pressor amines.

Marplan should be used cautiously in hyperactive or agitated patients, as well as in schizophrenic patients, because it may cause excessive stimulation. Activation of mania/hypomania has been reported in a small proportion of patients with major affective disorder who were treated with marketed antidepressants.

Drug Interactions

See CONTRAINDICATIONS, WARNINGS, and PRECAUTIONS sections for information on drug interactions.

Marplan should be administered with caution to patients receiving Antabuse® (disulfiram, Wyeth-Ayerst Laboratories). In a single study, rats given high intraperitoneal doses of an MAO inhibitor plus disulfiram experienced severe toxicity, including convulsions and death.

Concomitant use of Marplan and other psychotropic agents is generally not recommended because of possible potentiating effects. This is especially true in patients who may subject themselves to an overdosage of drugs. If combination therapy is needed, careful consideration should be given to the pharmacology of all agents to be used. The monoamine oxidase inhibitory effects of Marplan may persist for a substantial period after discontinuation of the drug, and this should be borne in mind when another drug is prescribed following Marplan. To avoid potentiation, the physician wishing to terminate treatment with Marplan and begin therapy with another agent should allow for an interval of 10 days.

Carcinogenesis, Mutagenesis, Impairment of Fertility

Long-term studies to evaluate carcinogenic potential have not been conducted with this drug, and there is no information concerning mutagenesis or impairment of fertility.

Pregnancy

There is a pregnancy exposure registry that monitors pregnancy outcomes in women exposed to antidepressant, including MARPLAN, during pregnancy. Healthcare providers are encouraged to register patients by calling the National Pregnancy Registry for Antidepressants at 1-844-405-6185 or visiting online at http://womensmentalhealth.org/clinical-and-research-programs/pregnancyregistry/antidepressants

The potential reproductive toxicity of isocarboxazid has not been adequately evaluated in animals. It is also not known whether isocarboxazid can cause embryo/fetal harm when administered to a pregnant woman or can affect reproductive capacity. Marplan should be given to a pregnant woman only if clearly needed.

Nursing Mothers

Levels of excretion of isocarboxazid and/or its metabolites in human milk have not been determined, and effects on the nursing infant are unknown. Marplan should be used in women who are nursing only if clearly needed.

Pediatric Use

Marplan is not recommended for use in patients under 16 years of age, as safety and effectiveness in pediatric populations have not been demonstrated.

ADVERSE REACTIONS

Adverse Findings Observed in Short-Term, Placebo-Controlled Trials

Systematically collected data are available from only 86 patients exposed to Marplan, of whom only 52 received doses of ≥50 mg/day, including only 11 who were dosed at ≥60 mg/day. Because of the limited experience with systematically monitored patients receiving Marplan at the higher end of the currently recommended dose range of up to 60 mg/day, caution is indicated in patients for whom a dose of 40 mg/day is exceeded (see WARNINGS).

The table that follows enumerates the incidence, rounded to the nearest percent, of treatment emergent adverse events that occurred among 86 depressed patients who received Marplan at doses ranging from 20 to 80 mg/day in placebo-controlled trials of 6 weeks in duration. Events included are those occurring in 1% or more of patients treated with Marplan and for which the incidence in patients treated with Marplan was greater than the incidence in placebo-treated patients.

The prescriber should be aware that these figures cannot be used to predict the incidence of adverse events in the course of usual medical practice where patient characteristics and other factors differ from those which prevailed in clinical trials. Similarly, the cited frequencies cannot be compared with figures obtained from other clinical investigations involving different treatments, uses, and investigators. The cited figures, however, do provide the prescribing physician with some basis for estimating the relative contribution of drug and non-drug factors to the adverse event incidence rate in the population studied.

The commonly observed adverse event that occurred in Marplan patients with an incidence of 5% or greater and at least twice the incidence in placebo patients were nausea, dry mouth, and dizziness (see Table).

In three clinical trials for which the data were pooled, 4 of 85 (5%) patients who received placebo, 10 of 86 (12%) who received <50 mg of Marplan per day, and 1 of 52 (2%) who received ≥50 mg of Marplan per day prematurely discontinued treatment. The most common reasons for discontinuation were dizziness, orthostatic hypotension, syncope, and dry mouth.

Treatment-Emergent Adverse Events Incidence in Placebo-Controlled Clinical Trials with Marplan Doses of 40 to 80 mg/day^1
BODY SYSTEM/ ADVERSE EVENT | PLACEBO (N=85) | MARPLAN <50 mg (N=86) | MARPLAN ≥50 mg (N=52)^2
MISCELLANEOUS
Drowsy | 0 | 4% | 0%
Anxiety | 1 | 2% | 0%
Chills | 0% | 2% | 0%
Forgetful | 1% | 2% | 2%
Hyperactive | 0% | 2% | 0%
Lethargy | 0% | 2% | 2%
Sedation | 1% | 2% | 0%
Syncope | 0% | 2% | 0%
INTEGUMENTARY
Sweating | 0% | 2% | 2%
MUSCULOSKELETAL
Heavy feeling | 0% | 2% | 0%
CARDIOVASCULAR
Orthostatic hypotension | 1% | 4% | 4%
Palpitations | 1% | 2% | 0%
GASTROINTESTINAL
Dry mouth | 4% | 9% | 6%
Constipation | 6% | 7% | 4%
Nausea | 2% | 6% | 4%
Diarrhea | 1% | 2% | 0%
UROGENITAL
Impotence | 0% | 2% | 0%
Urinary frequency | 1% | 2% | 0%
Urinary hesitancy | 0% | 1% | 4%
CENTRAL NERVOUS SYSTEM
Headache | 13% | 15% | 6%
Insomnia | 4% | 4% | 6%
Sleep disturbance | 0% | 5% | 2%
Tremor | 0% | 4% | 4%
Myoclonic jerks | 0% | 2% | 0%
Paresthesia | 1% | 2% | 0%
SPECIAL SENSES
Dizziness | 14% | 29% | 15%

^1Events reported by at least 1% of patients treated with Marplan are presented, except for those that had an incidence on placebo greater than or equal to that on Marplan.

^2All patients also received Marplan at doses <50 mg.

Other Events Observed During the Post-marketing Evaluation of Marplan

Isolated cases of akathisia, ataxia, black tongue, coma, dysuria, euphoria, hematologic changes, incontinence, neuritis, photosensitivity, sexual disturbances, spider telangiectases, and urinary retention have been reported. These side effects sometimes necessitate discontinuation of therapy. In rare instances, hallucinations have been reported with high dosages, but they have disappeared upon reduction of dosage or discontinuation of therapy. Toxic amblyopia was reported in one psychiatric patient who had received isocarboxazid for about a year; no causal relationship to isocarboxazid was established. Impaired water excretion compatible with the syndrome of inappropriate secretion of antidiuretic hormone (SIADH) has been reported.

To report SUSPECTED ADVERSE REACTIONS, contact Validus Pharmaceuticals LLC at

1-866-982-5438 or FDA at 1-800-FDA-1088 or www.fda.gov/medwatch.

DRUG ABUSE AND DEPENDENCE

Controlled Substance Class

Marplan is not a controlled substance.

Physical and Psychological Dependence

Marplan has not been systematically studied in animals or humans for its potential for abuse, tolerance, or physical dependence. There have been reports of drug dependency in patients using doses of Marplan significantly in excess of the therapeutic range. Some of these patients had a history of previous substance abuse. The following withdrawal symptoms have been reported: restlessness, anxiety, depression, confusion, hallucinations, headache, weakness, and diarrhea. Consequently, physicians should carefully evaluate Marplan patients for history of drug abuse and follow such patients closely, observing them for signs of misuse or abuse (e.g., development of tolerance, incrementations of dose, drug-seeking behavior).

OVERDOSAGE

The lethal dose of Marplan in humans is not known. There has been one report of a fatality in a patient who ingested 400 mg of Marplan together with an unspecified amount of another drug. Symptoms: Major overdosage may be evidenced by tachycardia, hypotension, coma, convulsions, respiratory depression, sluggish reflexes, pyrexia, and diaphoresis; these signs may persist for 8 to 14 days. Treatment: General supportive measures should be used, along with immediate gastric lavage or emetics. If the latter are given, the danger of aspiration must be borne in mind. An adequate airway should be maintained, with supplemental oxygen if necessary. The mechanism by which amine-oxidase inhibitors produce hypotension is not fully understood, but there is evidence that these agents block the vascular bed response. Thus it is suggested that plasma may be of value in the management of this hypotension. Administration of pressor amines such as Levophed® (levarterenol bitartrate) may be of limited value (note that their effects may be potentiated by Marplan). Continue treatment for several days until homeostasis is restored. Liver function studies are recommended during the 4 to 6 weeks after recovery, as well as the time of overdosage.

In managing overdosage, consider the possibility of multiple drug involvement. The physician should consider contacting a poison control center on the treatment of any overdose.

DOSAGE AND ADMINISTRATION

For maximum therapeutic effect, the dosage of Marplan must be individually adjusted on the basis of careful observation of the patient. Dosage should be started with one tablet (10 mg) of Marplan twice daily. If tolerated, dosage may be increased by increments of one tablet (10 mg) every 2 to 4 days to achieve a dosage of four tablets daily (40 mg) by the end of the first week of treatment. Dosage can then be increased by increments of up to 20 mg/week, if needed and tolerated, to a maximum recommended dosage of 60 mg/day. Daily dosage should be divided into two to four dosages. After maximum clinical response is achieved, an attempt should be made to reduce the dosage slowly over a period of several weeks without jeopardizing the therapeutic response. Beneficial effect may not be seen in some patients for 3 to 6 weeks. If no response is obtained by then, continued administration is unlikely to help.

Because of the limited experience with systematically monitored patients receiving Marplan at the higher end of the currently recommended dose range of up to 60 mg/day, caution is indicated in patients for whom a dose of 40 mg/day is exceeded (see ADVERSE REACTIONS).

HOW SUPPLIED

Marplan tablets 10 mg are peach colored, round and scored with "MARPLAN 10" imprinted on one side and scored on the other. Supplied in bottles of 100 (NDC 30698-032-01).

Storage: Store at 77ºF (25ºC); excursions permitted to 59º to 86ºF (15º to 30ºC) [See USP Controlled Room Temperature].

Dispense in a tight, light-resistant container as defined in USP.

Rx Only

Manufactured for and Distributed by:
Validus Pharmaceuticals LLC
Parsippany, NJ 07054
info@validuspharma.com
www.validuspharma.com
1-866-982-5438

© 2023 Validus Pharmaceuticals LLC All rights reserved

60009-09 April 2023

Medication Guide

Marplan® Tablets

(isocarboxazid)

Antidepressant Medicines, Depression and other Serious Mental Illnesses,

and Suicidal Thoughts or Actions

Read the Medication Guide that comes with your or your family member’s antidepressant medicine. This Medication Guide is only about the risk of suicidal thoughts and actions with antidepressant medicines. Talk to your or your family member’s, healthcare provider about:

- all risks and benefits of treatment with antidepressant medicines
- all treatment choices for depression or other serious mental illness

What is the most important information I should know about antidepressant medicines, depression and other serious mental illnesses, and suicidal thoughts or actions?

1. Antidepressant medicines may increase suicidal thoughts or actions in some children, teenagers, and young adults within the first few months of treatment.

2. Depression and other serious mental illnesses are the most important causes of suicidal thoughts and actions. Some people may have a particularly high risk of having suicidal thoughts or actions. These include people who have (or have a family history of) bipolar illness (also called manic-depressive illness) or suicidal thoughts or actions.

3. How can I watch for and try to prevent suicidal thoughts and actions in myself or a family member?

- Pay close attention to any changes, especially sudden changes, in mood, behaviors, thoughts, or feelings. This is very important when an antidepressant medicine is started or when the dose is changed.
- Call the healthcare provider right away to report new or sudden changes in mood, behavior, thoughts, or feelings.
- Keep all follow-up visits with the healthcare provider as scheduled. Call the healthcare provider between visits as needed, especially if you have concerns about symptoms.

Call a healthcare provider right away if you or your family member has any of the following symptoms, especially if they are new, worse, or worry you:

- thoughts about suicide or dying
- attempts to commit suicide
- new or worse depression
- new or worse anxiety
- feeling very agitated or restless
- panic attacks
- trouble sleeping (insomnia)
- new or worse irritability
- acting aggressive, being angry, or violent
- acting on dangerous impulses
- an extreme increase in activity and talking (mania)
- other unusual changes in behavior or mood

What else do I need to know about antidepressant medicines?

- Never stop an antidepressant medicine without first talking to a healthcare provider. Stopping an antidepressant medicine suddenly can cause other symptoms.
- Antidepressants are medicines used to treat depression and other illnesses. It is important to discuss all the risks of treating depression and also the risks of not treating it. Patients and their families or other caregivers should discuss all treatment choices with the healthcare provider, not just the use of antidepressants.
- Antidepressant medicines have other side effects. Talk to the healthcare provider about the side effects of the medicine prescribed for you or your family member.
- Antidepressant medicines can interact with other medicines. Know all of the medicines that you or your family member takes. Keep a list of all medicines to show the healthcare provider. Do not start new medicines without first checking with your healthcare provider.
- Not all antidepressant medicines prescribed for children are FDA approved for use in children. Talk to your child’s healthcare provider for more information.
- Tell your healthcare provider if you are pregnant or plan to become pregnant during treatment with Marplan.
  ○ If you become pregnant during treatment with Marplan, talk to your healthcare provider about registering with the National Pregnancy Registry for Antidepressants. You can register by calling 1-844-405-6185 or visit http://womensmentalhealth.org/clinical-and-research-programs/pregnancyregistry/antidepressants

This Medication Guide has been approved by the U.S. Food and Drug Administration.

Manufactured for and Distributed by:
Validus Pharmaceuticals LLC
Parsippany, NJ 07054
info@validuspharma.com
www.validuspharma.com
1-866-982-5438

© 2023 Validus Pharmaceuticals LLC All rights reserved

60143-03 April 2023

PRINCIPAL DISPLAY PANEL

NDC 30698-032-01
MARPLAN®
(isocarboxazid)
10 mg
100 Tablets
Rx Only